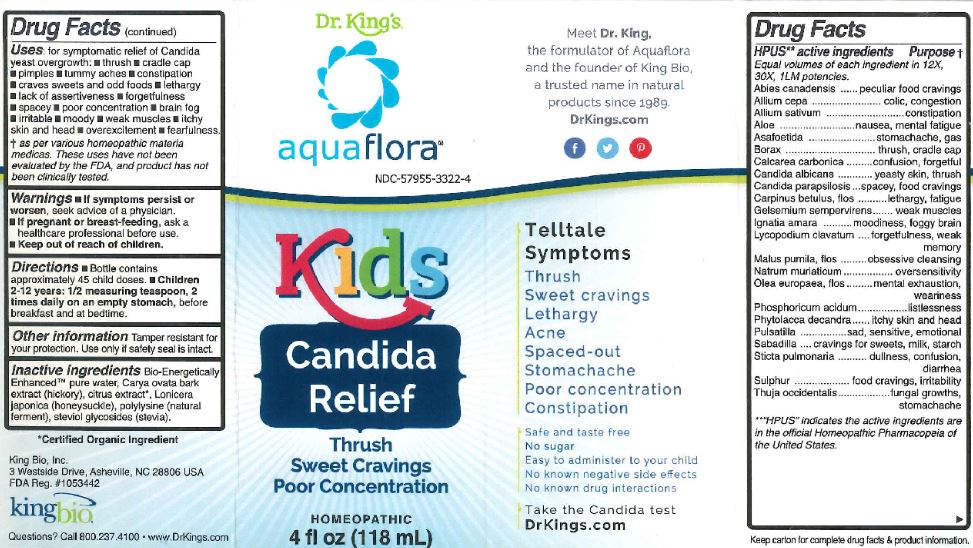 DRUG LABEL: Kids Candida Relief
NDC: 57955-3322 | Form: LIQUID
Manufacturer: King Bio Inc.
Category: homeopathic | Type: HUMAN OTC DRUG LABEL
Date: 20180601

ACTIVE INGREDIENTS: TSUGA CANADENSIS BARK 12 [hp_X]/118 mL; ONION 12 [hp_X]/118 mL; GARLIC 12 [hp_X]/118 mL; ALOE 12 [hp_X]/118 mL; FERULA ASSA-FOETIDA RESIN 12 [hp_X]/118 mL; SODIUM BORATE 12 [hp_X]/118 mL; OYSTER SHELL CALCIUM CARBONATE, CRUDE 12 [hp_X]/118 mL; CANDIDA ALBICANS 12 [hp_X]/118 mL; CANDIDA PARAPSILOSIS 12 [hp_X]/118 mL; CARPINUS BETULUS FLOWERING TOP 12 [hp_X]/118 mL; GELSEMIUM SEMPERVIRENS ROOT 12 [hp_X]/118 mL; STRYCHNOS IGNATII SEED 12 [hp_X]/118 mL; LYCOPODIUM CLAVATUM SPORE 12 [hp_X]/118 mL; MALUS PUMILA FLOWER 12 [hp_X]/118 mL; SODIUM CHLORIDE 12 [hp_X]/118 mL; OLEA EUROPAEA FLOWER 12 [hp_X]/118 mL; PHOSPHORIC ACID 12 [hp_X]/118 mL; PHYTOLACCA AMERICANA ROOT 12 [hp_X]/118 mL; ANEMONE PULSATILLA 12 [hp_X]/118 mL; SCHOENOCAULON OFFICINALE SEED 12 [hp_X]/118 mL; LOBARIA PULMONARIA 12 [hp_X]/118 mL; SULFUR 12 [hp_X]/118 mL; THUJA OCCIDENTALIS LEAFY TWIG 12 [hp_X]/118 mL
INACTIVE INGREDIENTS: WATER; CARYA OVATA BARK; CITRUS BIOFLAVONOIDS; LONICERA JAPONICA FLOWER; POLYEPSILON-LYSINE (4000 MW); REBAUDIOSIDE A

Kids Candida Relief

HPUS Active Ingredients

Abies canadensis, Allium cepa, Allium sativum, Aloe, Asafoetida, Borax, Calcarea carboica, Candida albicans, Candida parapsilosis, Carpinus betulus, flos, Gelsemium sempervirens, Ignatia amara, Lycopodium clavatum, Malus pumila, flos, Natrum muriaticum, Olea europaea, flos, Phosphoricum acidum, Phytolacca decandra, Pulsatilla, Sabadilla, Sticta pulmonaria, Sulphur, Thuja occidentalis

Uses:

for symptomatic relief of Candida yeast overgrowth:

- thrush
- cradle cap
- pimples
- tummy aches
- constipation
- craves sweets and odd foods
- lethargy
- lack of assertiveness
- forgetfulness
- spacey
- poor concentration
- brain fog
- irritable
- moody
- weak muscles
- itchy skin and head
- overexcitement
- fearfulness.

Purpose

Abies canadensis..................peculiar food cravins

Allium cepa...........................colic,congestion

Allium sativum.......................constipation

Aloe......................................nausea, mental fatigue

Asafoetida.............................stomacheache, gas

Borax....................................thrush, cradle cap

Calcarea carboica...................confusion, forgetful

Candida albicans......................yeasty skin, thrush

Candida parapsilosis................spacey, food cravings

Carpinus betulus, flos...............lethargy, fatigue

Gelsemium sempervirens.........weak muscles

Ignatia amara..........................moodiness, foggy brain

Lycopodium clavatum..............forgetfulness, weak

Malus pumila, flos....................obsessive cleansing

Natrum muriaticum..................ovesnsitivity

Olea europaea, flos..................menal exhaustion, weariness

Phosphoricum acidum..............listlessness

Phytolacca decandra................itchy skin and head

Pulsatilla..................................sad, sensitive, emotional

Sabadilla..................................cravings for sweets, milk, starch

Sticta pulmonaria......................dullness, confusion

Sulphur....................................food cravings, irritability

Thuja occidentalis.....................fungal gowths, stomachache

Warnings

- If symptoms persist or worsen, seek advice of a physician.
- If pregnant or breast-feeding, ask a healthcare professional before use.

Keep out of reach of children.

Directions

- Bottle contain approximately 45 child doses.
- Children 2-12 years: 1/2 measuring teaspoon, 2 times daily on an empty stomach, before beakfast and at bedtime.

Other Information

Tamper resistant for your proection. Use only if safety seal is intact

Inactive Ingredients

Bio-Energetically Enhanced pure water, Carya ovata bark extract (hickory), citrus extract, Lonicera Japonica (honeysuckle), polylysine (natural ferment), steviol glycosides (stevia).